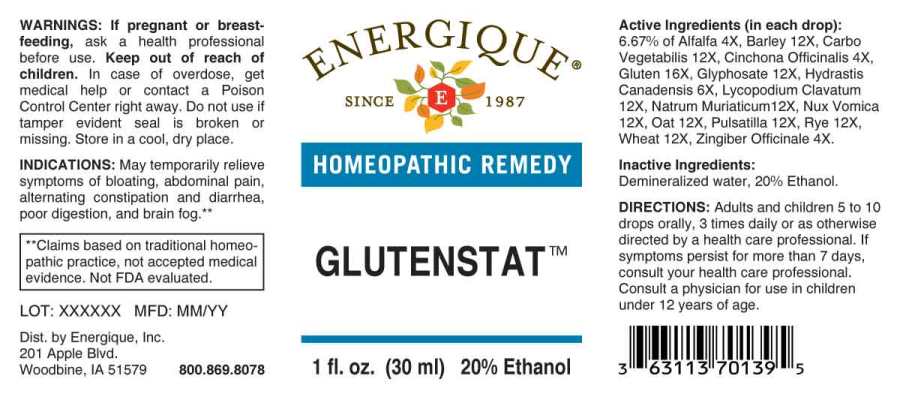 DRUG LABEL: Glutenstat
NDC: 44911-0670 | Form: LIQUID
Manufacturer: Energique, Inc.
Category: homeopathic | Type: HUMAN OTC DRUG LABEL
Date: 20230405

ACTIVE INGREDIENTS: MEDICAGO SATIVA WHOLE 4 [hp_X]/1 mL; GINGER 4 [hp_X]/1 mL; CINCHONA OFFICINALIS BARK 6 [hp_X]/1 mL; GOLDENSEAL 6 [hp_X]/1 mL; BARLEY 12 [hp_X]/1 mL; ACTIVATED CHARCOAL 12 [hp_X]/1 mL; GLYPHOSATE 12 [hp_X]/1 mL; LYCOPODIUM CLAVATUM SPORE 12 [hp_X]/1 mL; SODIUM CHLORIDE 12 [hp_X]/1 mL; STRYCHNOS NUX-VOMICA SEED 12 [hp_X]/1 mL; OAT 12 [hp_X]/1 mL; PULSATILLA VULGARIS WHOLE 12 [hp_X]/1 mL; RYE 12 [hp_X]/1 mL; WHEAT 12 [hp_X]/1 mL; WHEAT GLUTEN 16 [hp_X]/1 mL
INACTIVE INGREDIENTS: WATER; ALCOHOL

DRUG FACTS:

ACTIVE INGREDIENTS:

(in each drop): 6.67% of Alfalfa 4X, Barley 12X, Carbo Vegetabilis 12X, Cinchona Officinalis 4X, Gluten 16X, Glyphosate 12X, Hydrastis Canadensis 6X, Lycopodium Clavatum 12X, Natrum Muriaticum 12X, Nux Vomica 12X, Oat 12X, Pulsatilla 12X, Rye 12X, Wheat 12X, Zingiber Officinale 4X.

PURPOSE:

May temporarily relieve symptoms of bloating, abdominal pain, alternating constipation and diarrhea, poor digestion and brain fog.**

**Claims based on traditional homeopathic practice, not accepted medical evidence. Not FDA evaluated.

WARNINGS:

If pregnant or breast-feeding, ask a health professional before use.

Keep out of reach of children. In case of overdose, get medical help or contact a Poison Control Center right away.

Do not use if tamper evident seal is broken or missing.

Store in cool, dry place.

KEEP OUT OF REACH OF CHILDREN:

In case of overdose, get medical help or contact a Poison Control Center right away.

DIRECTIONS:

Adults and children 5 to 10 orally, 3 times daily or as otherwise directed by a health care professional. If symptoms persist for more than 7 days, consult your health care professional. Consult a physician for use in children under 12 years of age.

INDICATIONS:

May temporarily relieve symptoms of bloating, abdominal pain, alternating constipation and diarrhea, poor digestion and brain fog.**

**Claims based on traditional homeopathic practice, not accepted medical evidence. Not FDA evaluated.

INACTIVE INGREDIENTS:

Demineralized water, 20% Ethanol.

QUESTIONS:

Dist. by Energique, Inc.

201 Apple Blvd

Woodbine, IA 51579 800-869-8078

PACKAGE LABEL DISPLAY:

ENERGIQUE

SINCE 1987

HOMEOPATHIC REMEDY

GLUTENSTAT

1 fl. oz. (30 ml)